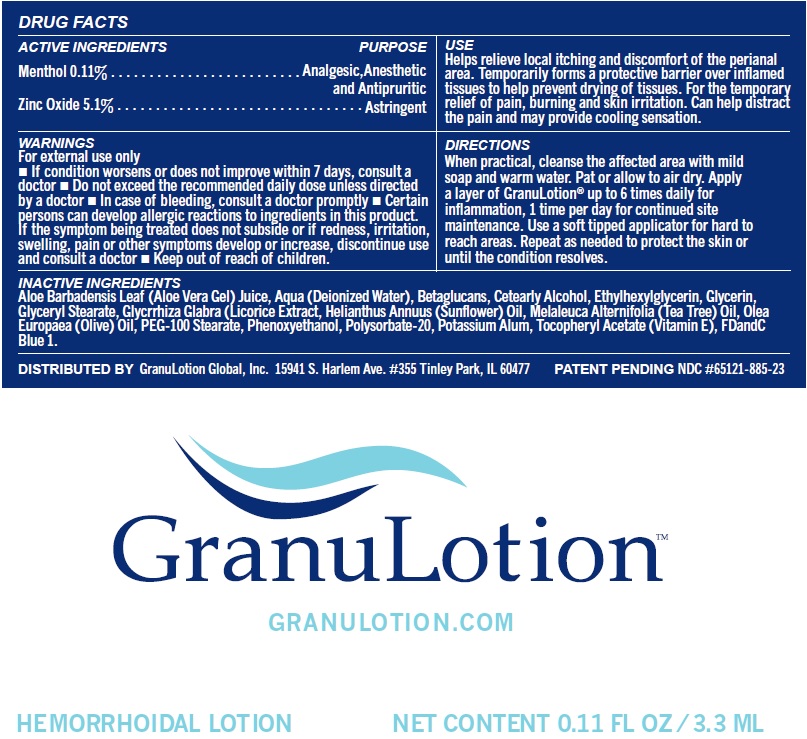 DRUG LABEL: GRANULOTION Hemorrhoidal
NDC: 82897-293 | Form: LOTION
Manufacturer: GL Health, Inc.
Category: otc | Type: HUMAN OTC DRUG LABEL
Date: 20260119

ACTIVE INGREDIENTS: MENTHOL 1.1 mg/1 mL; ZINC OXIDE 51 mg/1 mL
INACTIVE INGREDIENTS: ALOE VERA LEAF; WATER; CETOSTEARYL ALCOHOL; ETHYLHEXYLGLYCERIN; GLYCERIN; GLYCERYL MONOSTEARATE; LICORICE; HELIANTHUS ANNUUS FLOWERING TOP; TEA TREE OIL; OLIVE OIL; PEG-100 STEARATE; PHENOXYETHANOL; POLYSORBATE 20; POTASSIUM ALUM; .ALPHA.-TOCOPHEROL ACETATE; FD&C BLUE NO. 1

GRANULOTION Hemorrhoidal Lotion

ACTIVE INGREDIENTS

Menthol 0.11%

Zinc Oxide 5.1%

PURPOSE

Analgesic, Anesthetic and Antipruritic

Astringent

USE

Helps relieve local itching and discomfort of the perianal area. Temporarily forms a protective barrier over inflamed tissues to help prevent drying of tissues. For the temporary relief of pain, burning and skin irritation. Can help distract the pain and may provide cooling sensation.

WARNINGS

For external use only

- If condition worsens or does not improve within 7 days, consult a doctor
- Do not exceed the recommended daily dose unless directed by a doctor
- In case of bleeding, consult a doctor promptly
- Certain persons can develop allergic reactions to ingredients in this product. If the symptom being treated does not subside or if redness, irritation, swelling, pain or other symptoms develop or increase, discontinue use and consult a doctor

DIRECTIONS

When practical, cleanse the affected area with mild soap and warm water. Pat or allow to air dry. Apply a layer of GranuLotion® up to 6 times daily for inflammation, 1 time per day for continued site maintenance. Use a soft tipped applicator for hard to reach areas. Repeat as needed to protect the skin or until the condition resolves.

INACTIVE INGREDIENTS

Aloe Barbadensis Leaf (Aloe Vera Gel) Juice, Aqua (Deionized Water), Betaglucans, Cetearly Alcohol, Ethylhexylglycerin, Glycerin, Glyceryl Stearate, Glycrrhiza Glabra (Licorice Extract, Helianthus Annuus (Sunflower) Oil, Melaleuca Alternifolia (Tea Tree) Oil, Olea Europaea (Olive) Oil, PEG-100 Stearate, Phenoxyethanol, Polysorbate-20, Potassium Alum, Tocopheryl Acetate (Vitamin E), FDandC Blue 1.